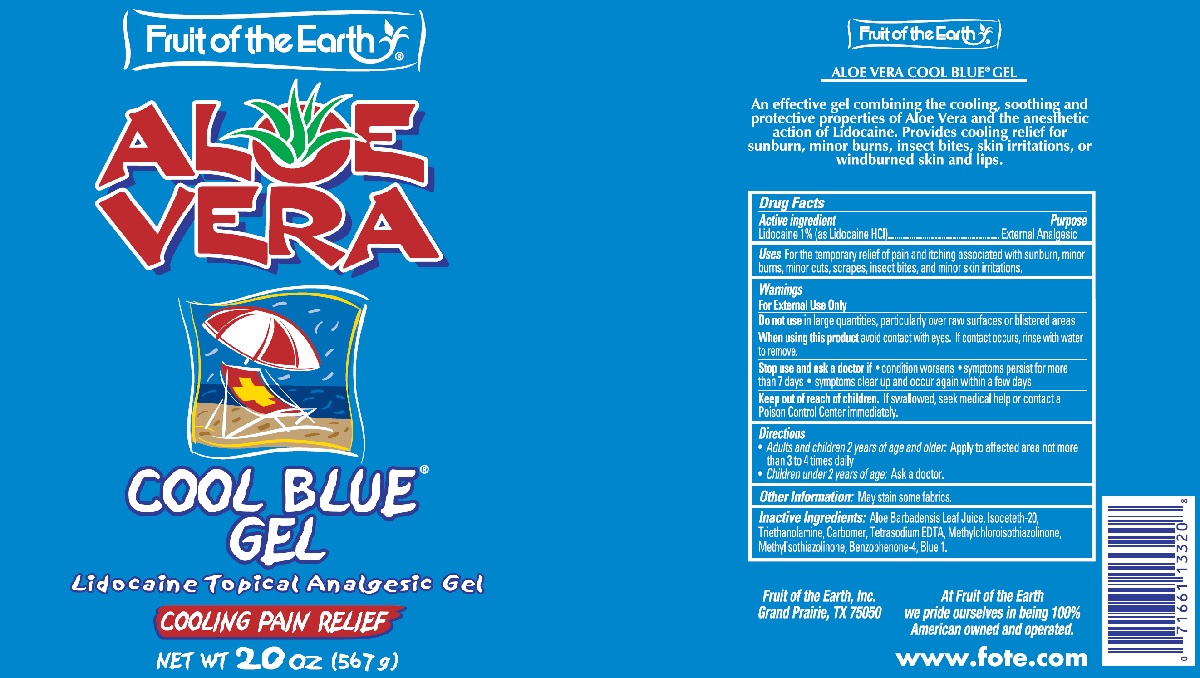 DRUG LABEL: Fruit of the Earth Aloe Vera Cool Blue
NDC: 62217-200 | Form: GEL
Manufacturer: Fruit of the Earth, Inc.
Category: otc | Type: HUMAN OTC DRUG LABEL
Date: 20240719

ACTIVE INGREDIENTS: LIDOCAINE 10 mg/1 g
INACTIVE INGREDIENTS: ALOE VERA LEAF; ISOCETETH-20; TROLAMINE; CARBOMER HOMOPOLYMER TYPE C; EDETATE SODIUM; FD&C BLUE NO. 1; METHYLCHLOROISOTHIAZOLINONE; METHYLISOTHIAZOLINONE; SULISOBENZONE

Fruit of the Earth Aloe Vera Cool Blue Gel

Active Ingredients

Lidocaine 1.0% (as Lidocaine HCl)

Purpose

External Analgesic

Uses

For the temporary relief of pain and itching associated with sunburn, minor burns, minor cuts, scrapes, insect bites, and minor skin irritations.

Warnings

- For External Use Only

DO NOT USE

Do not usein large quantities, particularly over raw surfaces or blistered areas

WHEN USING

When using this productavoid contact with eyes. If contact occurs, rinse with water to remove.

Stop use and ask a doctor if

- condition worsens
- symptoms persist for more than 7 days
- symptoms clear up and occur again within a few days

Keep out of reach of children.If swallowed, seek medical help or contact a Poison Control Center immediately.

Directions

- Adults and children 2 years of age and older:Apply to affected area not more than 3 to 4 times daily
- Children under 2 years of age:Ask a doctor.

Other Information:May stain some fabrics.

Inactive Ingredients

Aloe Barbadensis Leaf Juice, Isoceteth-20, Triethanolamine, Carbomer, Tetrasodium EDTA, Methylchloroisothiazolinone, Methylisothiazolinone, Benzophenone-4, Blue 1.

PACKAGE LABEL

Fruit of the Earth

Aloe Vera

Cool Blue Gel

567 grams

NDC: 62217-200-20